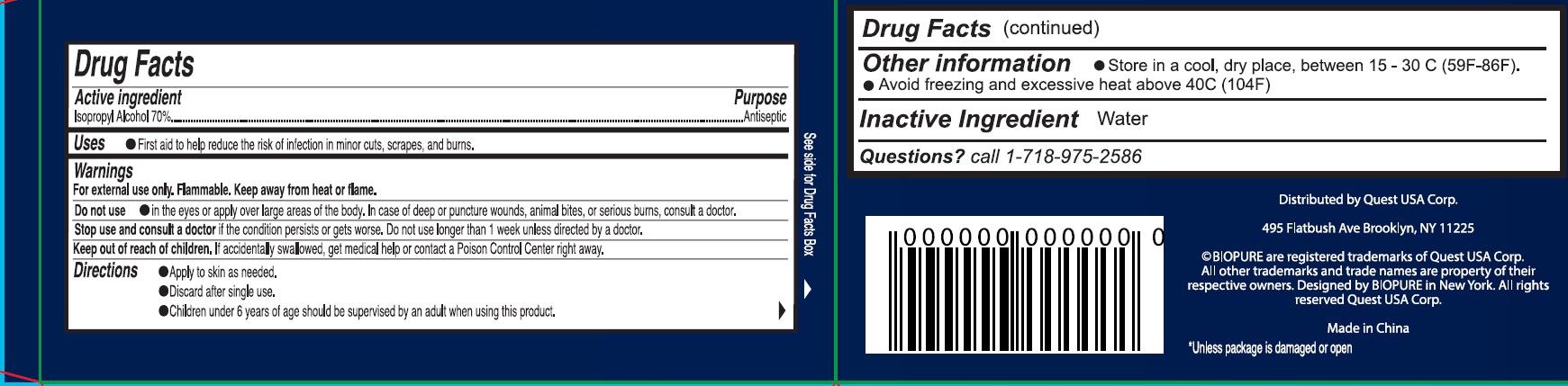 DRUG LABEL: Biopure alcohol prep pads 70 isopropyl
NDC: 78691-025 | Form: LIQUID
Manufacturer: Quest USA Corp
Category: otc | Type: HUMAN OTC DRUG LABEL
Date: 20240917

ACTIVE INGREDIENTS: ISOPROPYL ALCOHOL 70 mL/100 mL
INACTIVE INGREDIENTS: WATER

Biopure alcohol prep pads 70 % isopropyl

Active ingredient

Isopropyl Alcohol 70%

Purpose

Antiseptic

Uses

- First aid to help reduce the risk of infection in minor cuts, scrapes, and burns.

Warnings

For external use only. Flammable. Keep away from heat or flame.

Do not use

- in the eyes or apply over large areas of the body. In case of deep or puncture wounds, animal bites, or serious burns, consult a doctor.

Stop use and consult a doctor

if the condition persists or gets worse. Do not use longer than 1 week unless directed by a doctor.

Keep out of reach of children.

If accidentally swallowed, get medical help or contact a Posion Control Center right away.

Directions

- Apply to skin as needed.
- Discard after single use.
- Children under 6 years of age should be supervised by an adult when using this product.

Other information

- Store in a cool, dry place, between 15 - 30 C (59F-86F).
- Avoid freezing and excessive heat above 40C (104F)

Inactive Ingredient

Water

Questions?

call 1-718-975-2586